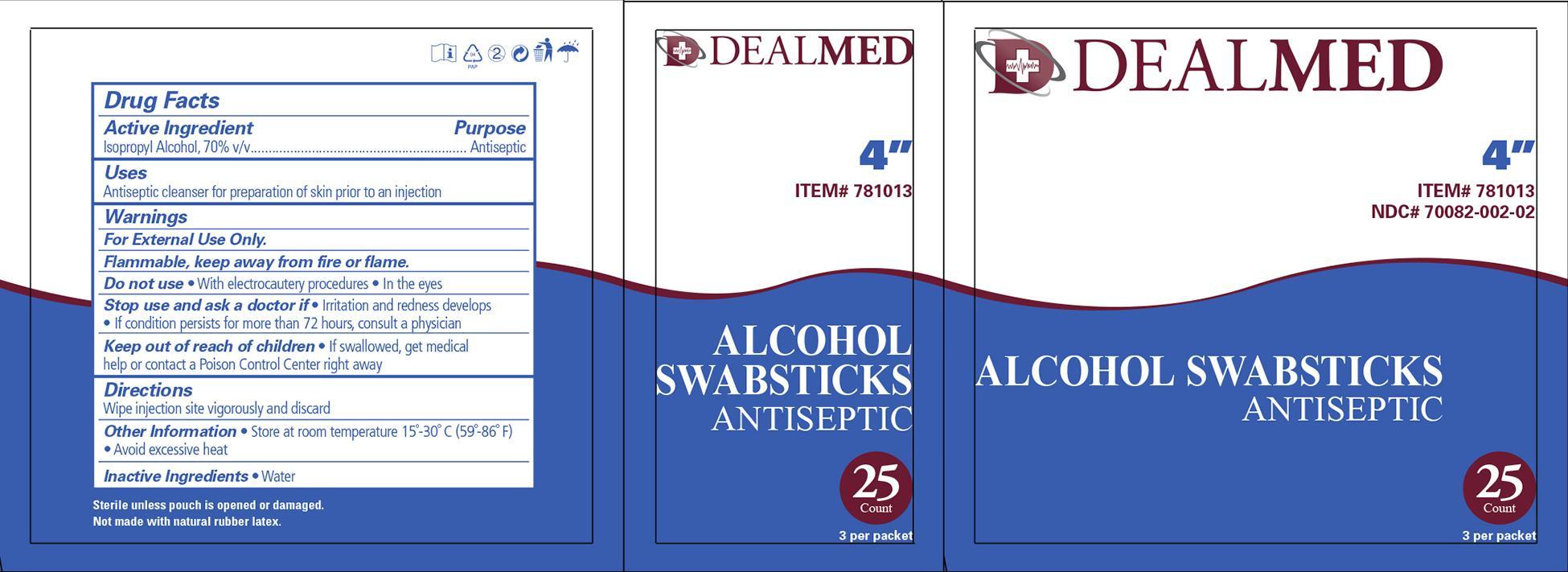 DRUG LABEL: Alcohol
NDC: 70082-002 | Form: SWAB
Manufacturer: Dealmed Medical Supplies LLC
Category: otc | Type: HUMAN OTC DRUG LABEL
Date: 20241216

ACTIVE INGREDIENTS: ISOPROPYL ALCOHOL 0.7 mL/1 mL
INACTIVE INGREDIENTS: WATER

DM-1203 Dealmed Alcohol Swabsticks NDC 70082-002-01
DM-1204 Dealmed Alcohol Swabsticks NDC 70082-002-02

Active Ingredient Purpose

Isopropyl Alcohol 70% v/v Antiseptic

Use:

For preparation of the skin prior to injection.

Warnings:

- For external use only
- Flammable, keep away from flame or fire
- Not for use with electrocautinary devices or procedures
- Do not use in eyes

Indications and Usage:

Stop use and ask a doctor if:

- Irritation or redness develops
- condition persists for more than 72 hours
- Cleansing of an injection site

Keep out of reach of children.

In case of accidental ingestion, seek professional assistance or consult a poison control center immediately.

Directions:

Wipe injection site vigorously and discard

Other information:

- Store at room temperature: 15 deg C to 30 deg C 59 deg F to 86 deg F
- avoid excessive heat

Inactive Ingredient

- Water

Principal Display Panel

Dealmed Alcohol Swabstick